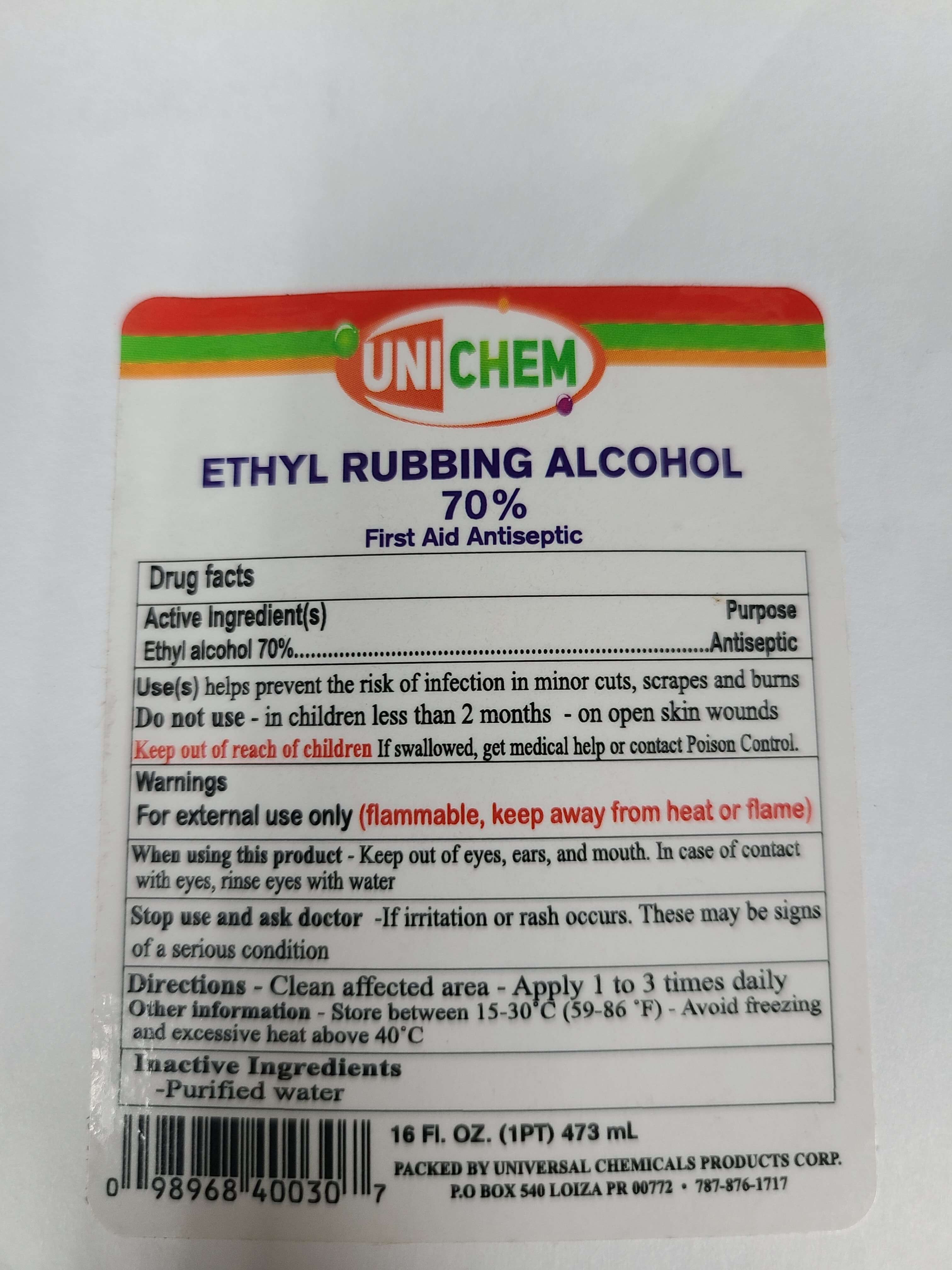 DRUG LABEL: UNICHEM
NDC: 82150-770 | Form: LIQUID
Manufacturer: Universal Chemical Products, Corp.
Category: otc | Type: HUMAN OTC DRUG LABEL
Date: 20210831

ACTIVE INGREDIENTS: ALCOHOL 72.5 mL/100 mL
INACTIVE INGREDIENTS: GLUTARALDEHYDE 0.03 mL/100 mL; WATER 26.75 mL/100 mL; ISOPROPYL ALCOHOL 0.75 mL/100 mL

Ethyl Rubbing Alcohol 70%

Active Ingredient(s)

Ehtyl Alcohol 70% v/v. Purpose: Antiseptic

Purpose

Antiseptic

Use

Helps prevent the risk of infection in minor cuts, scrapes and burns.

Warnings

For external use only. Flammable. Keep away from heat or flame

Do not use

- in children less than 2 months of age
- on open skin wounds

When using this product keep out of eyes, ears, and mouth. In case of contact with eyes, rinse eyes thoroughly with water.
Stop use and ask a doctor if irritation or rash occurs. These may be signs of a serious condition.
Keep out of reach of children. If swallowed, get medical help or contact a Poison Control Center right away.

Stop use and ask a doctor if irritation or rash occurs. These may be signs of a serious condition.

Keep out of reach of children. If swallowed, get medical help or contact a Poison Control Center right away.

Directions

- Clean affected area
- Supervise children under 6 years of age when using this product to avoid swallowing.

Other information

- Store between 15-30C (59-86F)
- Avoid freezing and excessive heat above 40C (104F)

Inactive ingredients

Glutaraldehyde, purified water USP, Isopropyl Alcohol

Changes made to use the Hand Sanitizer template to register Regular Isopropyl Alcohol Products.

Section 3: Use(Indications & Usage Section):

For cleaning minor cuts and preventing infections. It is not to subtitue when water or soap isn't readily available.

Date: june/2020

Package Label - Principal Display Panel

473 mL NDC: 82150-770-16